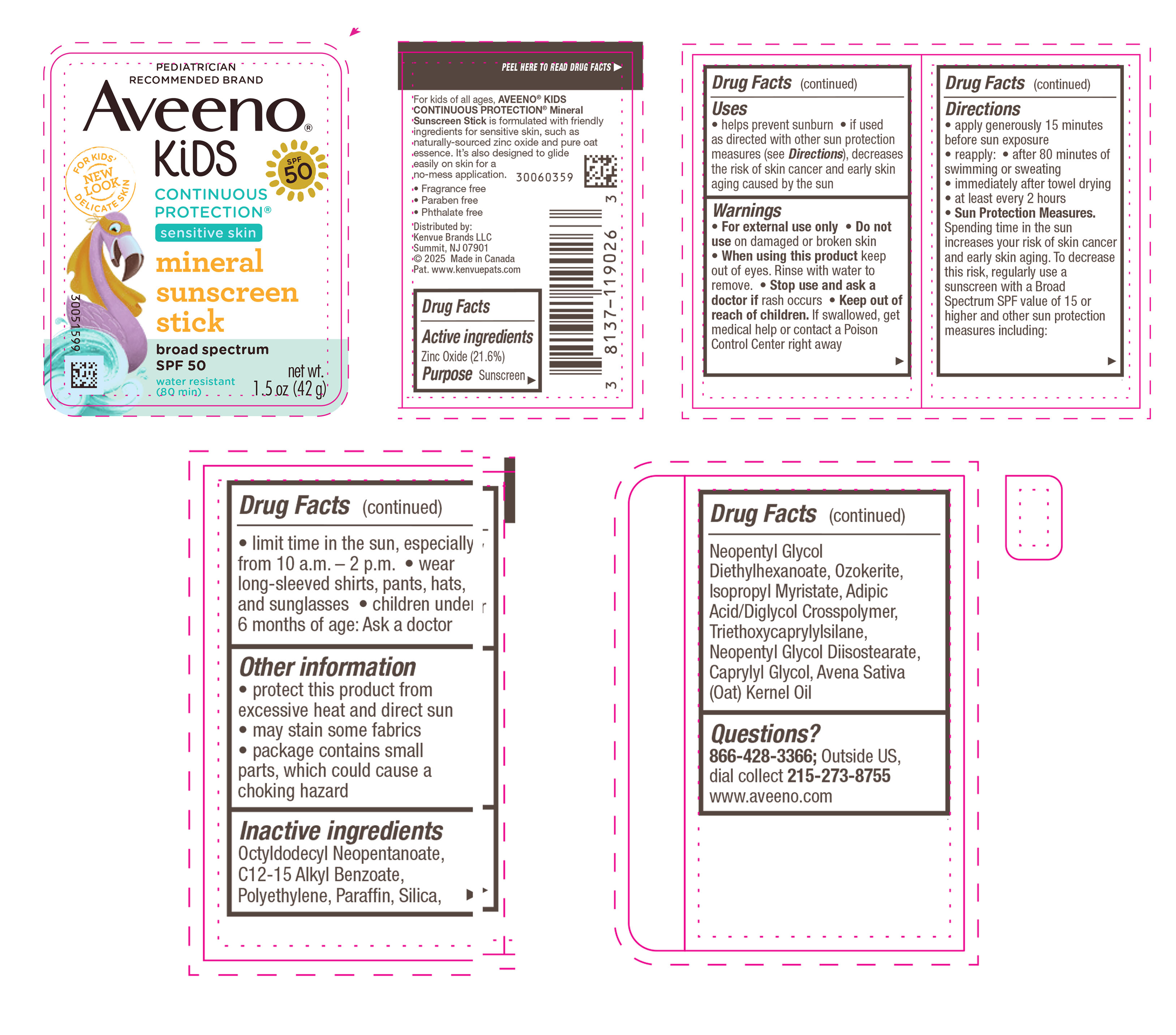 DRUG LABEL: Aveeno Kids Continuous Protection Sensitive Skin Mineral Sunscreen Broad Spectrum SPF 50
NDC: 69968-0602 | Form: STICK
Manufacturer: Kenvue Brands LLC
Category: otc | Type: HUMAN OTC DRUG LABEL
Date: 20250618

ACTIVE INGREDIENTS: ZINC OXIDE 216 mg/1 g
INACTIVE INGREDIENTS: POLYETHYLENE; OCTYLDODECYL NEOPENTANOATE; ALKYL (C12-15) BENZOATE; PARAFFIN; SILICON DIOXIDE; NEOPENTYL GLYCOL DIETHYLHEXANOATE; CERESIN; ISOPROPYL MYRISTATE; ADIPIC ACID/DIGLYCOL CROSSPOLYMER (20000 MPA.S); TRIETHOXYCAPRYLYLSILANE; NEOPENTYL GLYCOL DIISOSTEARATE; CAPRYLYL GLYCOL; OAT KERNEL OIL

Aveeno® Kids Continuous Protection® Sensitive Skin Mineral Sunscreen Stick Broad Spectrum SPF 50

Drug Facts

Active ingredients

Zinc Oxide (21.6%)

Purpose

Sunscreen

Uses

- helps prevent sunburn
- if used as directed with other sun protection measures (see Directions), decreases the risk of skin cancer and early skin aging caused by the sun

Warnings

For external use only

Do not use on damaged or broken skin

- When using this product keep out of eyes. Rinse with water to remove.

Stop use and ask a doctor if rash occurs

Keep out of reach of children. If swallowed, get medical help or contact a Poison Control Center right away.

Directions

- apply generously 15 minutes before sun exposure
- reapply:
  - after 80 minutes of swimming or sweating
  - immediately after towel drying
  - at least every 2 hours
- Sun Protection Measures. Spending time in the sun increases your risk of skin cancer and early skin aging. To decrease this risk, regularly use a sunscreen with a Broad Spectrum SPF value of 15 or higher and other sun protection measures including:
  - limit time in the sun, especially from 10 a.m. – 2 p.m.
  - wear long-sleeved shirts, pants, hats, and sunglasses
- children under 6 months of age: Ask a doctor

Other information

- protect this product from excessive heat and direct sun
- may stain some fabrics
- package contains small parts, which could cause a choking hazard

Inactive ingredients

Octyldodecyl Neopentanoate, C12-15 Alkyl Benzoate, Polyethylene, Paraffin, Silica, Neopentyl Glycol Diethylhexanoate, Ozokerite, Isopropyl Myristate, Adipic Acid/Diglycol Crosspolymer, Triethoxycaprylylsilane, Neopentyl Glycol Diisostearate, Caprylyl Glycol, Avena Sativa (Oat) Kernel Oil

Questions?

866-428-3366; Outside US, dial collect 215-273-8755 www.aveeno.com

Distributed by:

Kenvue Brands LLC

Summit, NJ 07901

PRINCIPAL DISPLAY PANEL - 42 g Canister Label

PEDIATRICIAN

RECOMMENDED BRAND

Aveeno®

KiDS

FOR KIDS’

NEW

LOOK

DELICATE SKIN

SPF

50

CONTINUOUS

PROTECTION®

sensitive skin

mineral

sunscreen

stick

broad spectrum

SPF 50

water resistant

(80 min)

net wt.

1.5 oz (42 g)